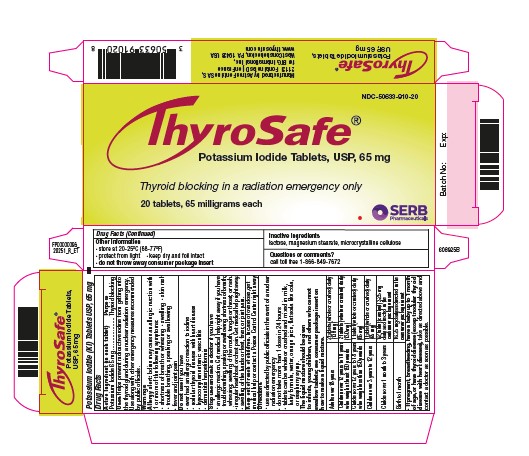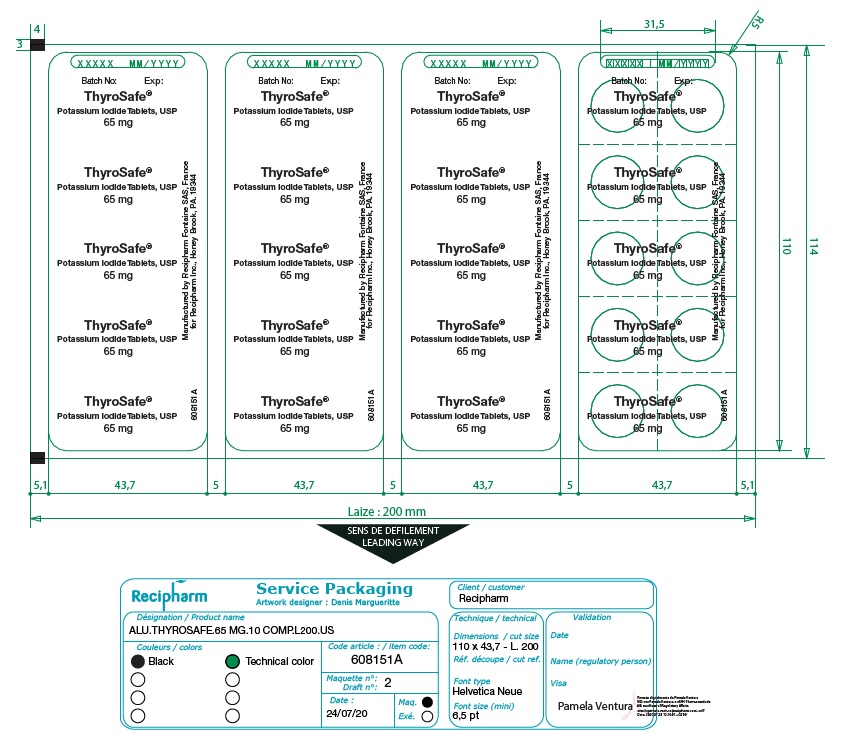 DRUG LABEL: ThyroSafe
NDC: 50633-910 | Form: TABLET
Manufacturer: BTG International Inc.
Category: otc | Type: HUMAN OTC DRUG LABEL
Date: 20251217

ACTIVE INGREDIENTS: POTASSIUM IODIDE 65 mg/1 1
INACTIVE INGREDIENTS: LACTOSE, UNSPECIFIED FORM; MICROCRYSTALLINE CELLULOSE; MAGNESIUM STEARATE

BOXED WARNING

Take potassium iodide (KI) only when public officials tell you. In a nuclear radiation emergency, radioactive iodine could be released into the air. KI protects only the thyroid gland from uptake of radioactive iodine. Therefore, KI should be used along with other emergency measures that will be recommended to you by public officials. If you are told to take this medicine, take it 1 time every 24 hours. Do not take it more often. More KI will not help you. Too much KI may increase the chances of side effects. Do not take this medicine if you know you are allergic to iodine (see SIDE EFFECTSbelow).

ACTIVE INGREDIENT

DESCRIPTION

Each white, round, cross-scored ThyroSafe® tablet contains 65 mg of potassium iodide.

PURPOSE

INDICATIONS

ThyroSafe® (Potassium Iodide Tablets, USP) is a thyroid blocking medicine that is used in a nuclear radiation emergency only.

INDICATIONS AND USAGE

DIRECTIONS FOR USE

Use only as directed by public officials if a nuclear radiation emergency happens.

DOSAGE AND ADMINISTRATION

Dose:

Adults over 18 years | 2 tablets (whole or crushed) every day (130 mg)
Children over 12 years to 18 years who weigh at least 150 pounds | 2 tablets (whole or crushed) every day (130 mg)
Children over 12 years to 18 years who weigh less than 150 pounds | 1 tablet (whole or crushed) or 8 teaspoons every day (65 mg)
Children over 3 years to 12 years | 1 tablet (whole or crushed) or 8 teaspoons every day (65 mg)
Children over 1 month to 3 years | 4 teaspoons every day (32.5 mg)
Babies at birth to 1 month | 2 teaspoons every day (16.25 mg)

Tablets can be crushed and mixed in many liquids. To take the tablet in liquid solution, use dosing directions under Making a Potassium Iodide Liquid Mixture.

Take KI every day (every 24 hours) as directed by public officials. Do not take more than 1 dose in 24 hours. More will not help you. Too much medicine may increase the chances of side effects.

Making a Potassium Iodide Liquid Mixture:

1. Put one65 mg KI tablet into a small bowl and grind it into a fine powder using the back of a metal teaspoon against the inside of the bowl. The powder should not have any large pieces.
2. Add 4 teaspoons of water to the crushed KI powder in the bowl and mix until the KI powder is dissolved in the water.
3. Take the KI water mixture solution made in step 2 and mix it with 4 teaspoons of low fat white or chocolate milk, orange juice, flat soda, raspberry syrup, or infant formula.
4. The KI liquid mixture will keep for up to 7 days in the refrigerator. It is recommended that the KI liquid mixtures be prepared weekly. Throw away unused portions.

The amount of KI (65 mg tablet) in the drink when mixed as described above is 8.125 mg per teaspoon. The number of teaspoons of the drink to give your child depends on your child’s age as described in the following table:

Child’s Age | Give your child this amount in teaspoons
Over 12 to 18 years old who weigh less than 150 pounds | 8 teaspoons will give you a 65 mg dose
Over 3 to 12 years old | 8 teaspoons will give you a 65 mg dose
Over 1 month to 3 years old | 4 teaspoons will give you a 32.5 mg dose
Birth to 1 month | 2 teaspoons will give you a 16.25 mg dose

Note: This is the amount to give your child for onesingle dose in teaspoons (nottablespoons). You should give your child onedose each day as recommended by the public officials.

Pregnant or breastfeeding women or babies under 1 month of age:Take as directed above and call a doctor as soon as possible. Repeat dosing should be avoided. It is recommended that thyroid function be checked in babies less than 1 month of age that take KI. Women who are pregnant or breastfeeding should also be checked by a doctor if repeat dosing is necessary. Although these precautions should be taken, the benefits of short-term use of KI to block uptake of radioactive iodine by the thyroid gland far exceed its chances of side effects.

Patients with thyroid disease:If you have both a nodular thyroid condition such as multinodular goiter with heart disease, you should not take KI. Patients with other thyroid conditions may take KI as directed above, but call a doctor if you need to take KI for more than a few days.

WARNING

People who are allergic to iodine, have dermatitis herpetiformis or hypocomplementemic vasculitis, or have nodular thyroid disease with heart disease should not take KI. Keep out of the reach of children. In case of an allergic reaction (difficulty breathing, speaking or swallowing; wheezing; shortness of breath or swelling of the mouth or throat), call 911 or get medical care right away. In case of overdose, get medical help or call a Poison Control Center right away.

HOW POTASSIUM IODIDE WORKS

Certain forms of iodine help your thyroid gland work right. Most people get the iodine they need from foods like iodized salt or fish. The thyroid can "store" or hold only a certain amount of iodine.

In a nuclear radiation emergency, radioactive iodine may be released in the air. This material may be breathed or swallowed. It may enter the thyroid gland and damage it. The damage would probably not show itself for years. Children are most likely to have thyroid damage.

If you take KI, it will block or reduce the chances that radioactive iodine will enter your thyroid gland.

WHO SHOULD NOT TAKE POTASSIUM IODIDE

People should avoid KI if they are allergic to iodine, have dermatitis herpetiformis or hypocomplementemic vasculitis, or have nodular thyroid disease with heart disease, because these conditions may increase the chances of side effects to iodine.

HOW AND WHEN TO TAKE POTASSIUM IODIDE

KI should be taken as soon as possible after public officials tell you. If you are told to repeat the dose, you should take the second dose 24 hours after the first dose. Do not take it sooner. More KI will not help you because the thyroid can "hold" only certain amounts of iodine. Taking more than 1 dose per day will increase the chances of side effects. The public officials will tell you how many days to take KI. You should take KI until the chances of major exposure to radioactive iodine by breathing or swallowing stops.

SIDE EFFECTS

Short-term use of KI at the recommended dose is safe. You should not take this drug for longer than you are told.

Possible side effects include: swelling of the salivary glands, nausea, vomiting, diarrhea, stomach ache, fever, headache, metallic taste, and allergic reactions. Allergic reactions can include

- skin rashes such as hives
- swelling of various parts of the body such as the face, lips, tongue, throat, hands or feet
- fever with joint pain
- trouble breathing, speaking or swallowing
- wheezing or shortness of breath

Get medical attention right away if you have trouble breathing, speaking or swallowing; wheezing; shortness of breath; or swelling of the mouth, tongue or throat.

Taking iodide, in rare cases, may cause overactivity of the thyroid gland, underactivity of the thyroid gland, or enlargement of the thyroid gland (goiter). Symptoms of an overactive thyroid gland may include an irregular heart beat and chest pain. Patients with thyroid disease are more likely to get these side effects. Babies under 1 month of age are more likely to get an underactive thyroid gland (hypothyroidism).

WHAT TO DO IF SIDE EFFECTS OCCUR

Stop taking KI and call a doctor if you have one or more of the following symptoms:

- swelling of the face, hands or feet
- fever and joint pain
- skin rash

Stop taking KI and get medical help right away if you have one or more of the following symptoms:

- trouble breathing, speaking or swallowing
- shortness of breath or wheezing
- swelling of the lips, tongue or throat
- irregular heart beat or chest pain

HOW SUPPLIED

ThyroSafe® (potassium iodide, USP) tablets. Packages of 10 and 20 tablets. Each white, round, cross-scored tablet contains 65 mg potassium iodide. Store at 20-25° C (68-77° F). Keep dry and foil intact.

Manufactured by Astrea Fontaine SAS,
21121 Fontaine les Dijon, France
for BTG International Inc., West Conshohocken, PA 19428 USA
1-866-849-7672.
www.thyrosafe.com.

Revised 02/2022

Drug Facts
Other information

- store at 20-25° C (68-77° F)
- protect from light
- keep dry and foil intact
- do not throw away consumer package insert

Inactive ingredients
lactose, magnesium stearate, microcrystalline cellulose

Questions or comments?
call toll free 1-866-849-7672

KEEP OUT OF REACH OF CHILDREN

Carton Label - Principal Display Panel

NDC-50633-910-20

ThyroSafe®
Potassium Iodide Tablets, USP, 65 mg
Thyroid blocking in a radiation emergency only
20 tablets, 65 milligrams each

Carton Label – Back panel

Potassium Iodide (KI) Tablets USP, 65 mg

Drug Facts

Active Ingredient (in each tablet)
Potassium Iodide 65 mg

Purpose
Thyroid blocking

Usehelps prevent radioactive iodine from getting into the thyroid gland during a nuclear radiation emergency. Use along with other emergency measures recommended by public officials.

Warnings
Allergy alert: Iodine may cause an allergic reaction with 1 or more of the following symptoms:

- shortness of breath or wheezing
- swelling
- skin rash
- trouble breathing, speaking or swallowing
- fever and joint pain

Do not useif you have

- ever had an allergic reaction to iodine
- nodular thyroid disease with heart disease
- hypocomplementemic vasculitis
- dermatitis herpetiformis

Stop use and ask a doctor if you haveif you have

- allergic reaction. Get medical help right away if you have trouble breathing, speaking or swallowing; shortness of breath; wheezing; swelling of the mouth, tongue or throat; or rash.
- irregular heart or chest pain. Get medical help right away.
- swelling of the hands or feet, fever, or joint pain.

Keep out of reach of children.In case of overdose, get medical help or contact a Poison Control Center right away.

Directions

- use as directed by public officials in the event of a nuclear radiation emergency.
- do not take more than 1 dose in 24 hours.
- tablets can be whole or crushed and mixed in milk, baby formula, water, orange juice, flat soda like cola, or raspberry syrup.

The liquid mixture should be given to infants, young children, and others who cannot swallow tablets; see consumer package insert on how to make a liquid mixture.

adults over 18 years

2 tablets (whole or crushed) daily (130 mg)

children over 12 years to 18 years who weigh at least 150 pounds

2 tablets (whole or crushed) daily (130 mg)

children over 12 years to 18 years who weigh less than 150 pounds

1 tablet (whole or crushed) daily (65 mg)

children over 3 years to 12 years

1 tablet (whole or crushed) daily (65 mg)

children over 1 month to 3 years

1/2 tablet (crushed) 32.5 mg daily as directed in the consumer package insert

babies at birth to 1 month

16.25 mg daily as directed in consumer package insert

If pregnant, breastfeeding, have a baby up to 1 month of age, or have thyroid disease(except nodular thyroid disease with heart disease), take as directed above and contact a doctor as soon as possible

Principal Display Panel - 65 mg Carton Label

NDC-50633-910-20

ThyroSafe®

Potassium Iodide Tablets, USP, 65 mg

Thyroid blocking in a radiation emergency only

20 tablets, 65 milligrams each

BTG International Inc.